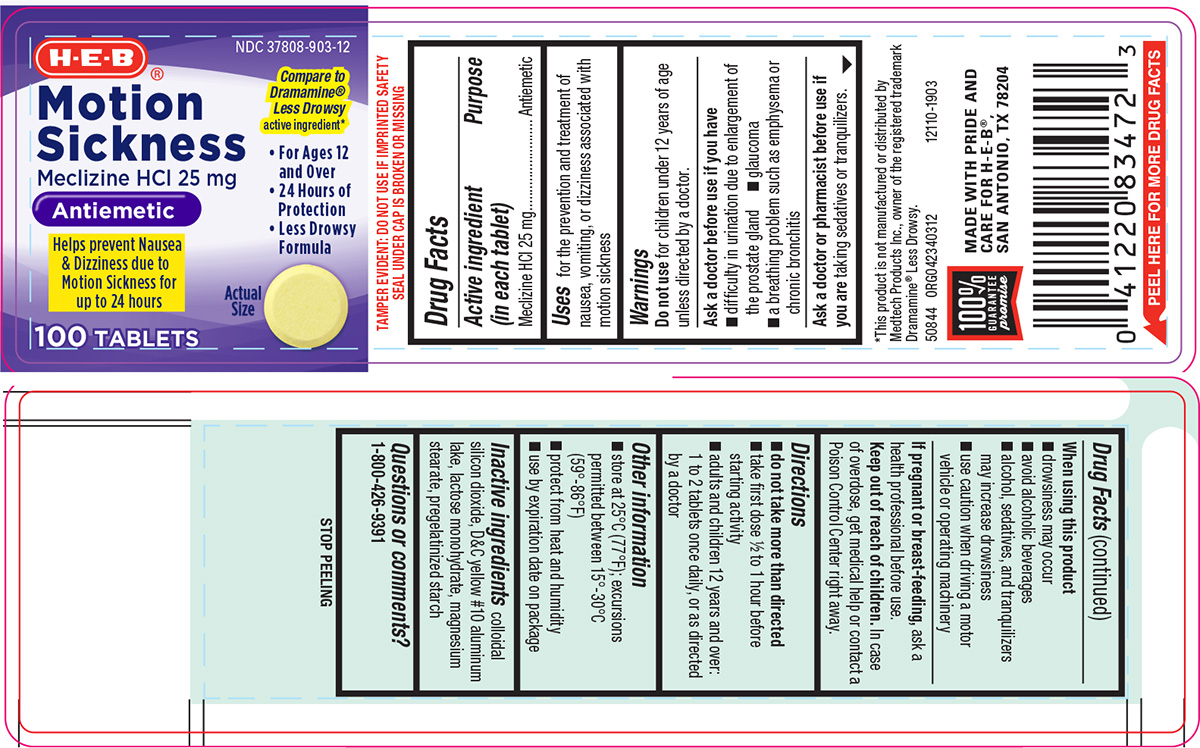 DRUG LABEL: Motion Sickness
NDC: 37808-903 | Form: TABLET
Manufacturer: H E B
Category: otc | Type: HUMAN OTC DRUG LABEL
Date: 20250808

ACTIVE INGREDIENTS: MECLIZINE HYDROCHLORIDE 25 mg/1 1
INACTIVE INGREDIENTS: SILICON DIOXIDE; D&C YELLOW NO. 10 ALUMINUM LAKE; LACTOSE MONOHYDRATE; MAGNESIUM STEARATE; STARCH, CORN

HEB 44-403A

Active ingredient (in each tablet)

Meclizine HCl 25 mg

Purpose

Antiemetic

Uses

for the prevention and treatment of nausea, vomiting, or dizziness associated with motion sickness

Warnings

Do not use

for children under 12 years of age unless directed by a doctor.

Ask a doctor before use if you have

- difficulty in urination due to enlargement of the prostate gland
- glaucoma
- a breathing problem such as emphysema or chronic bronchitis

Ask a doctor or pharmacist before use if you are

taking sedatives or tranquilizers.

When using this product

- drowsiness may occur
- avoid alcoholic beverages
- alcohol, sedatives, and tranquilizers may increase drowsiness
- use caution when driving a motor vehicle or operating machinery

If pregnant or breast-feeding,

ask a health professional before use.

Keep out of reach of children.

In case of overdose, get medical help or contact a Poison Control Center right away.

Directions

- do not take more than directed
- take first dose 1/2 to 1 hour before starting activity
- adults and children 12 years and over: 1 to 2 tablets once daily, or as directed by a doctor

Other information

- store at 25°C (77°F); excursions permitted between 15°-30°C (59°-86°F)
- protect from heat and humidity
- use by expiration date on package

Inactive ingredients

colloidal silicon dioxide, D&C yellow #10 aluminum lake, lactose monohydrate, magnesium stearate, pregelatinized starch

Questions or comments?

1-800-426-9391

Principal Display Panel

H-E-B®

NDC 37808-903-12

Compare to
Dramamine®
Less Drowsy
active ingredient*

Motion
Sickness
Meclizine HCl 25 mg

Antiemetic

Helps prevent Nausea
& Dizziness due to
Motion Sickness for
up to 24 hours

• For Ages 12 and Over
• 24 Hours of Protection
• Less Drowsy Formula

Actual
Size

100 TABLETS

TAMPER EVIDENT: DO NOT USE IF IMPRINTED SAFETY
SEAL UNDER CAP IS BROKEN OR MISSING

*This product is not manufactured or distributed by
Medtech Products Inc., owner of the registered trademark
Dramamine® Less Drowsy.
50844 ORG042340312

12110-1903

100%
GUARANTEE
promise

MADE WITH PRIDE AND
CARE FOR H-E-B®,
SAN ANTONIO, TX 78204

HEB 44-403A